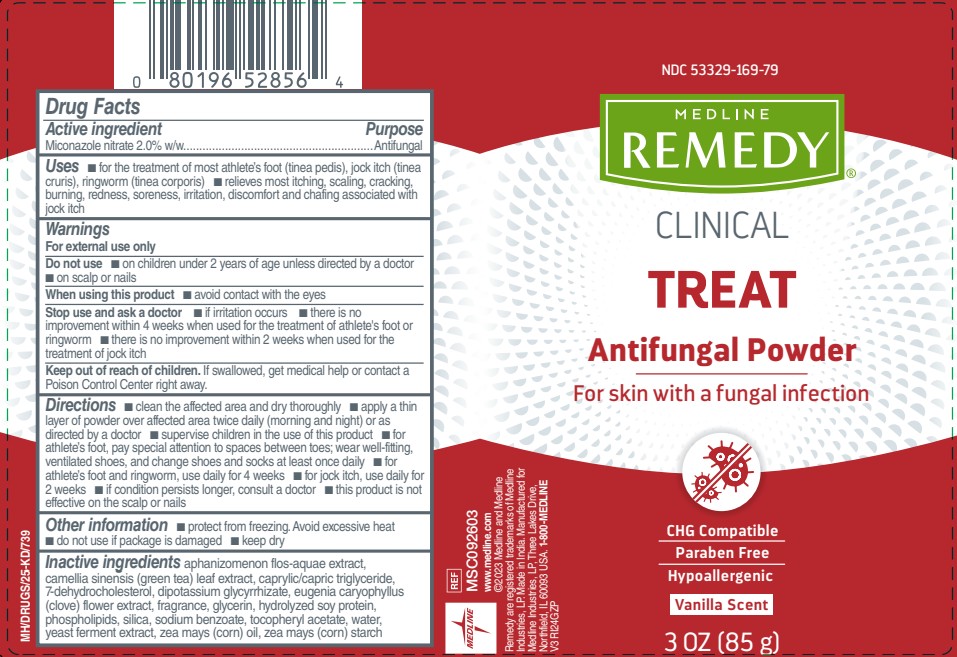 DRUG LABEL: Remedy Antifungal
NDC: 53329-169 | Form: POWDER
Manufacturer: Medline Industries, LP
Category: otc | Type: HUMAN OTC DRUG LABEL
Date: 20251029

ACTIVE INGREDIENTS: MICONAZOLE NITRATE 2 g/100 g
INACTIVE INGREDIENTS: APHANIZOMENON FLOS-AQUAE; GREEN TEA LEAF; CAPRYLIC/CAPRIC/LINOLEIC TRIGLYCERIDE; 7-DEHYDROCHOLESTEROL; GLYCYRRHIZINATE DIPOTASSIUM; ETHYLENE BRASSYLATE; CLOVE; GLYCERIN; SOY PROTEIN; ISOPROPYL MYRISTATE; METHYL DIHYDROJASMONATE (SYNTHETIC); EGG PHOSPHOLIPIDS; HYDRATED SILICA; SODIUM BENZOATE; .ALPHA.-TOCOPHEROL ACETATE; VANILLA; WATER; YEAST; CORN OIL; STARCH, CORN

169 Remedy Clinical Treat Antifungal Powder

Active ingredient

Miconazole nitrate 2.0% w/w

Purpose

Antifungal

Uses

- for the treatment of most athlete's foot (tinea pedis), jock itch (tinea cruris), ringworm (tinea corporis)
- relieves most itching, scaling, cracking, burning, redness, soreness, irritation, discomfort and chafing associated with jock itch

Warnings

For external use only

Do not use

- on children under 2 years of age unless directed by a doctor
- on scalp or nails

When using this product

avoid contact with the eyes

Stop use and ask a doctor

- if irritation occurs
- there is no improvement within 4 weeks when used for the treatment of athlete's foot or ringworm
- there is no improvement within 2 weeks when used for the treatment of jock itch

Keep out of reach of children

If swallowed, get medical help or contact a Poison Control center right away.

Directions

- Clean the affected area and dry thoroughly
- Apply a thin layer of powder over affected area twice daily (morning and night) or as directed by a doctor
- Supervise children in the use of this product
- For athlete's foot, pay special attention between spaces in toes; wear well-fitting, ventilated shoes, and change shoes and socks at least once daily
- For athlete's foot and ringworm, use daily for 4 weeks
- For jock itch, use daily for 2 weeks
- If condition persists longer, consult a doctor
- This product is not effective on the scalp or nails.

Other Information

- protect from freezing. Avoid excessive heat.
- do not use if package is damaged
- keep dry

Inactive ingredients

Aphanizomenon Flos-Aquae (Algae) Extract, Camellia Sinensis (Green Tea) Leaf Extract, Caprylic/Capric Triglycerides, 7-Dehydrocholesterol, Dipotassium Glycyrrhizate, Ethylene Brassylate, Eugenia Caryophyllus (Clove) Flower Extract, Fragrance, Glycerin, Hydrolyzed Soy Protein, Phospholipids, Silica, Sodium Benzoate, Tocopheryl Acetate, Water, Yeast Ferment Extract, Zea Mays (Corn) Oil, Zea Mays (Corn) Starch